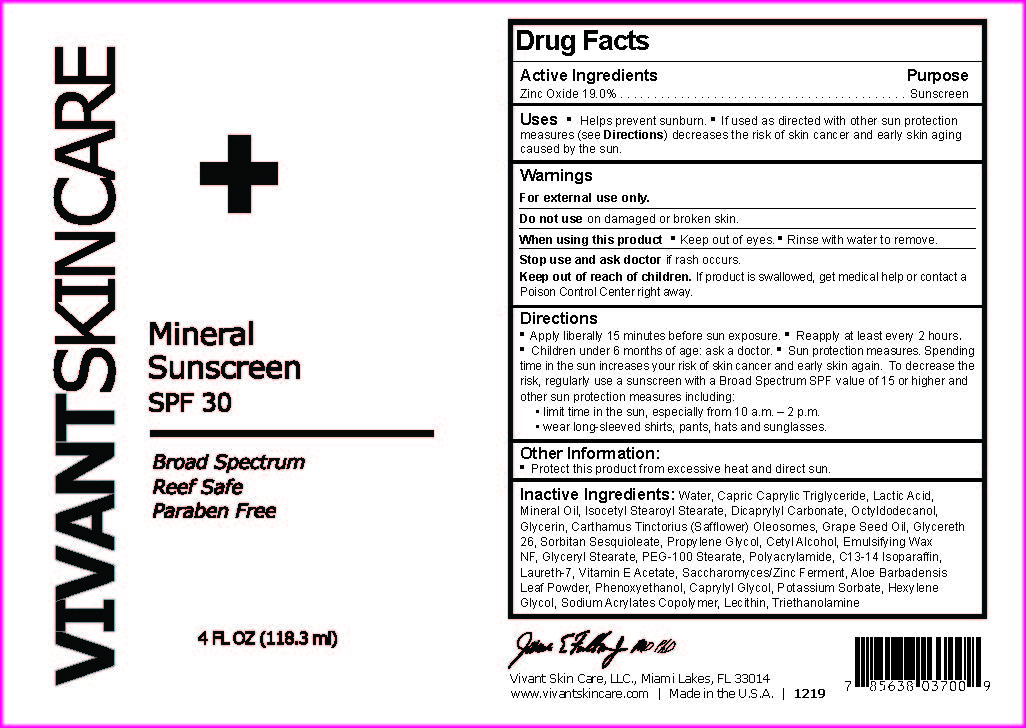 DRUG LABEL: Mineral Suscreen SPF 30
NDC: 63750-037 | Form: CREAM
Manufacturer: Vivant Pharmaceuticals, LLC
Category: otc | Type: HUMAN OTC DRUG LABEL
Date: 20250724

ACTIVE INGREDIENTS: ZINC OXIDE 22400 mg/118.3 mL
INACTIVE INGREDIENTS: GLYCERIN; MEDIUM-CHAIN TRIGLYCERIDES; HEXYLENE GLYCOL; LAURETH-7; POLYSORBATE 60; PEG-100 STEARATE; C13-14 ISOPARAFFIN; PHENOXYETHANOL; POTASSIUM SORBATE; WATER; PROPYLENE GLYCOL; SODIUM ACRYLATE; GLYCERYL MONOSTEARATE; YEAST; LECITHIN, SUNFLOWER; POLYACRYLAMIDE (10000 MW); ALOE VERA LEAF; .ALPHA.-TOCOPHEROL ACETATE; TROLAMINE; LACTIC ACID; MINERAL OIL; ISOCETYL STEAROYL STEARATE; DICAPRYLYL CARBONATE; OCTYLDODECANOL; CARTHAMUS TINCTORIUS (SAFFLOWER) OLEOSOMES; GRAPE SEED OIL; GLYCERETH-26; SORBITAN SESQUIOLEATE; CETYL ALCOHOL; CAPRYLYL GLYCOL

Vivant Skincare Sunscreen SPF 30

Active Ingredients

Zinc Oxide 19.0%

Purpose

Sunscreen

Uses

Helps prevent sunburn. If used as directed with other sun protection measures (see Directions) decreases the risk of skin cancer and early skin aging caused by the sun.

Warnings

For external use only.

Do not use on damaged or broken skin.

.

When using this product

Keep out of eyes. Rinse with water to remove.

Stop use and ask doctor

if rash occurs.

Keep out of reach of children.

If product is swallowed, get medical help or contact a Poison Control Center right away

Directions

Apply liberally 15 minutes before sun exposure. Reapply at least every 2 hours.

Children under 6 months of age: ask a doctor. Sun protection measures. Spending time in the sun increases your risk of skin cancer and early skin again. To decrease the risk, regularly use a sunscreen with a Broad Spectrum SPF value of 15 or higher and other sun protection measures including:

limit time in the sun, especially from 10 a.m. – 2 p.m.

wear long-sleeved shirts, pants, hats and sunglasses.

Other Information:

Protect this product from excessive heat and direct sun.

Inactive Ingredients:

Water, Capric Caprylic Triglyceride, Lactic Acid, Mineral Oil, Isocetyl Stearoyl Stearate, Dicaprylyl Carbonate, Octyldodecanol, Glycerin, Carthamus Tinctorius (Safflower) Oleosomes, Grape Seed Oil, Glycereth 26, Sorbitan Sesquioleate, Propylene Glycol, Cetyl Alcohol, Emulsifying Wax NF, Glyceryl Stearate, PEG-100 Stearate, Polyacrylamide, C13-14 Isoparaffin, Laureth-7, Vitamin E Acetate, Saccharomyces/Zinc Ferment, Aloe Barbadensis Leaf Powder, Phenoxyethanol, Caprylyl Glycol, Potassium Sorbate, Hexylene Glycol, Sodium Acrylates Copolymer, Lecithin, Triethanolamine